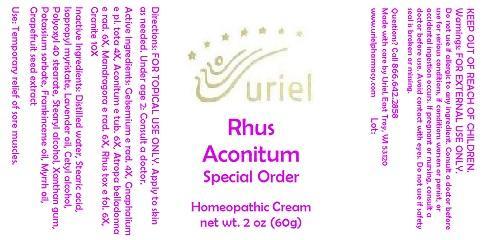 DRUG LABEL: Rhus Aconitum Special Order
NDC: 48951-8265 | Form: CREAM
Manufacturer: Uriel Pharmacy Inc.
Category: homeopathic | Type: HUMAN OTC DRUG LABEL
Date: 20140924

ACTIVE INGREDIENTS: GELSEMIUM SEMPERVIRENS ROOT 4 [hp_X]/1 g; PSEUDOGNAPHALIUM LUTEOALBUM LEAF 4 [hp_X]/1 g; ACONITUM NAPELLUS 6 [hp_X]/1 g; ATROPA BELLADONNA 6 [hp_X]/1 g; MANDRAGORA OFFICINARUM ROOT 6 [hp_X]/1 g; TOXICODENDRON PUBESCENS LEAF 6 [hp_X]/1 g; PENOXSULAM 10 [hp_X]/1 g
INACTIVE INGREDIENTS: WATER; STEARIC ACID; ISOPROPYL MYRISTATE; LAVENDER OIL; CETYL ALCOHOL; POLYOXYL 40 STEARATE; STEARYL ALCOHOL; XANTHAN GUM; POTASSIUM SORBATE; FRANKINCENSE OIL; MYRRH OIL; CITRUS PARADISI SEED

Rhus Aconitum Special Order

INDICATIONS AND USAGE

Directions: FOR TOPICAL USE ONLY.

DOSAGE AND ADMINISTRATION

Apply to skin as needed. Under age 2: Consult a doctor.

ACTIVE INGREDIENT

Active Ingredients: Gelsemium e rad. 4X, Gnaphalium e pl. tota 4X, Aconitum e tub. 6X, Atropa belladonna e rad. 6X, Mandragora e rad. 6X, Rhus tox e fol. 6X, Granite 10X

INACTIVE INGREDIENT

Inactive Ingredients: Distilled water, Stearic acid, Isopropyl myristate, Lavender oil, Cetyl alcohol, Polyoxyl 40 stearate, Stearyl alcohol, Xanthan gum, Potassium sorbate, Frankincense oil, Myrrh oil, Grapefruit seed extract

PURPOSE

Use: Temporary relief of sore muscles.

KEEP OUT OF REACH OF CHILDREN.

WARNINGS

Warnings: FOR EXTERNAL USE ONLY. Do not use if allergic to any ingredient. Consult a doctor before use for serious conditions, if conditions worsen or persist, or accidental ingestion occurs. If pregnant or nursing, consult a doctor before use. Avoid contact with eyes. Do not use if safety seal is broken or missing.

QUESTIONS

Questions? Call 866.642.2858 Made with care by Uriel, East Troy, WI 53120 www.urielpharmacy.com